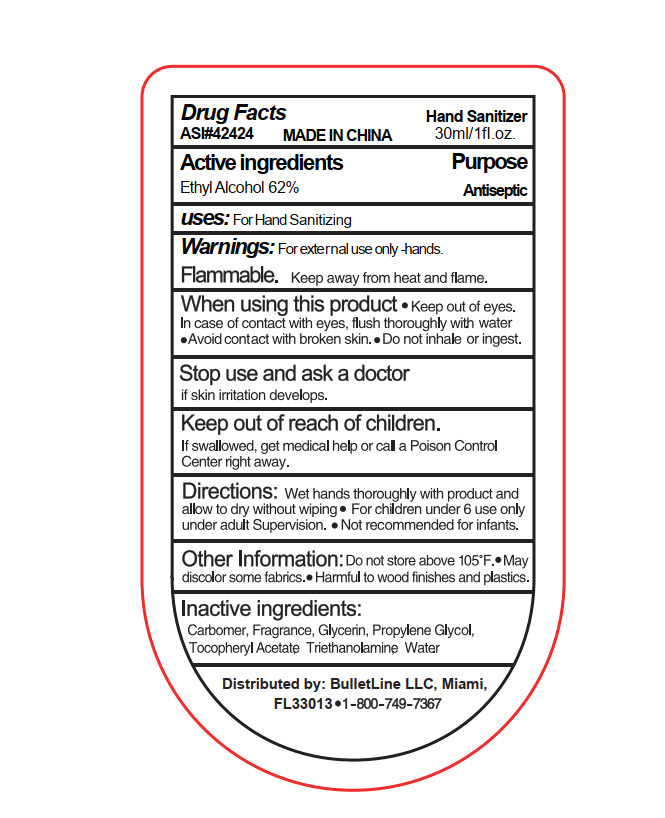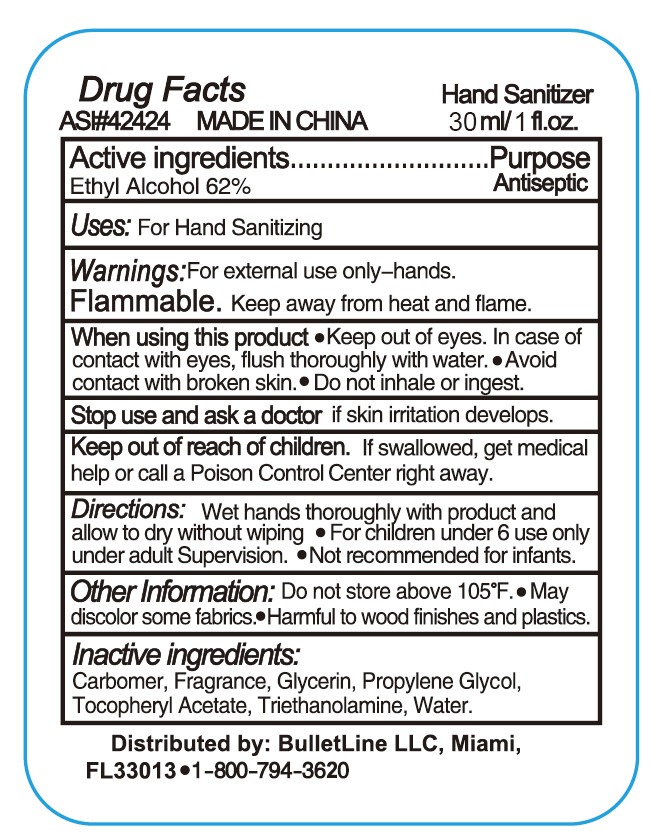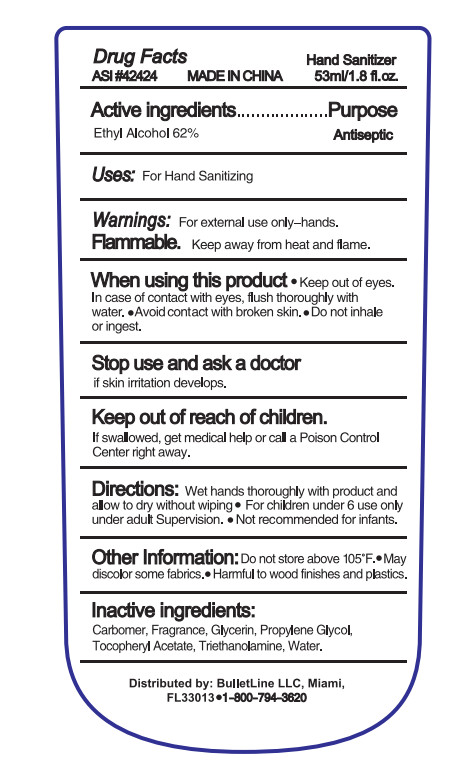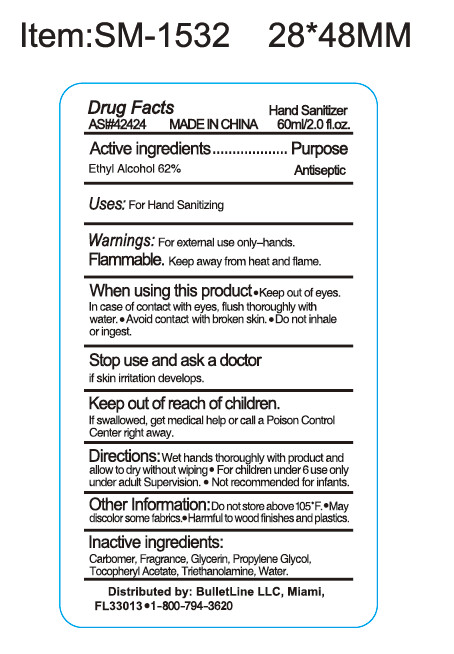 DRUG LABEL: Hand Sanitizer
NDC: 75209-009 | Form: GEL
Manufacturer: GUANGDONG MINGLIU TECHNOLOGY DAIL-USE CHEMICAL CO., LTD.
Category: otc | Type: HUMAN OTC DRUG LABEL
Date: 20200602

ACTIVE INGREDIENTS: ALCOHOL 62 mL/100 mL
INACTIVE INGREDIENTS: PROPYLENE GLYCOL; CARBOMER 934; FRAGRANCE LAVENDER & CHIA F-153480; WATER; TROLAMINE; GLYCERIN; .ALPHA.-TOCOPHEROL ACETATE

Hand Sanitizer

Active Ingredient(s)

Alcohol62%

Purpose

Antiseptic

Use

For Hand Sanitizing

Warnings

For external use only-hands.
Flammable. Keep away from heat and flame.

Do not use

/

WHEN USING

Keep out of eyes. In case of contact with eyes, flush thoroughly with water. Avoid contact with broken skin.

Do not inhale or ingest.

Stop use and ask a doctor if skin irritation develops.

Keep out of reach of children. If swallowed, get medical help or contact a Poison Control Center right away.

Directions

Wet hands thoroughly with product and allow to dry without wiping For children under 6 use only under adult Supervision. Not recommended for infants.

Other information

Do not store above105°F.
May discolor some fabrics.
Harmful to wood finishes and plastics.

Inactive ingredients

Carbomer, Fragrance, Glycerin, Propylene Glycol, Tocopheryl Acetate, Triethanolamine, Water